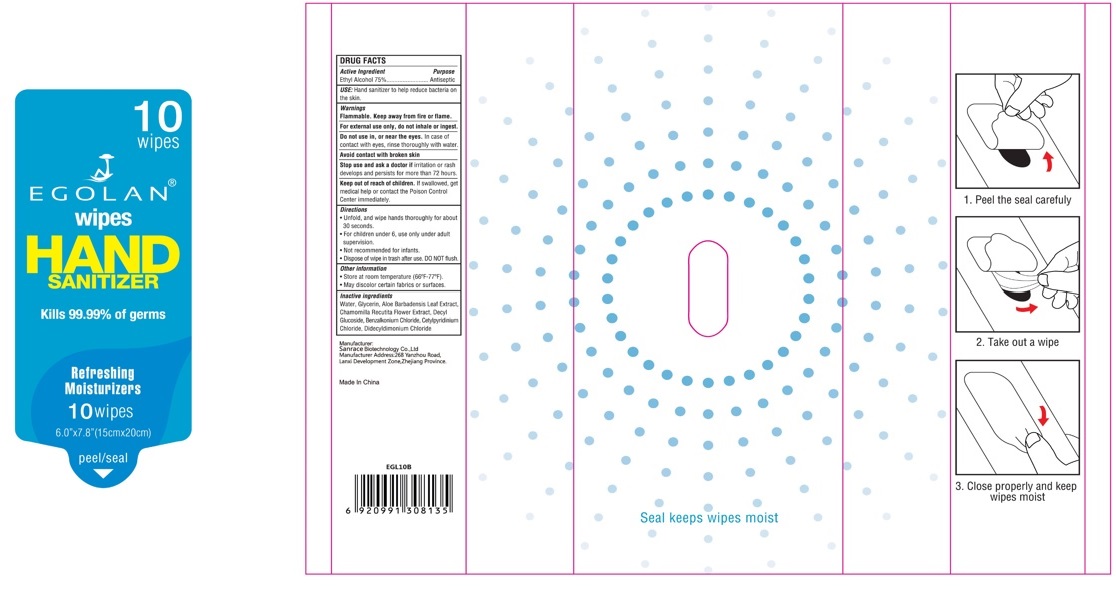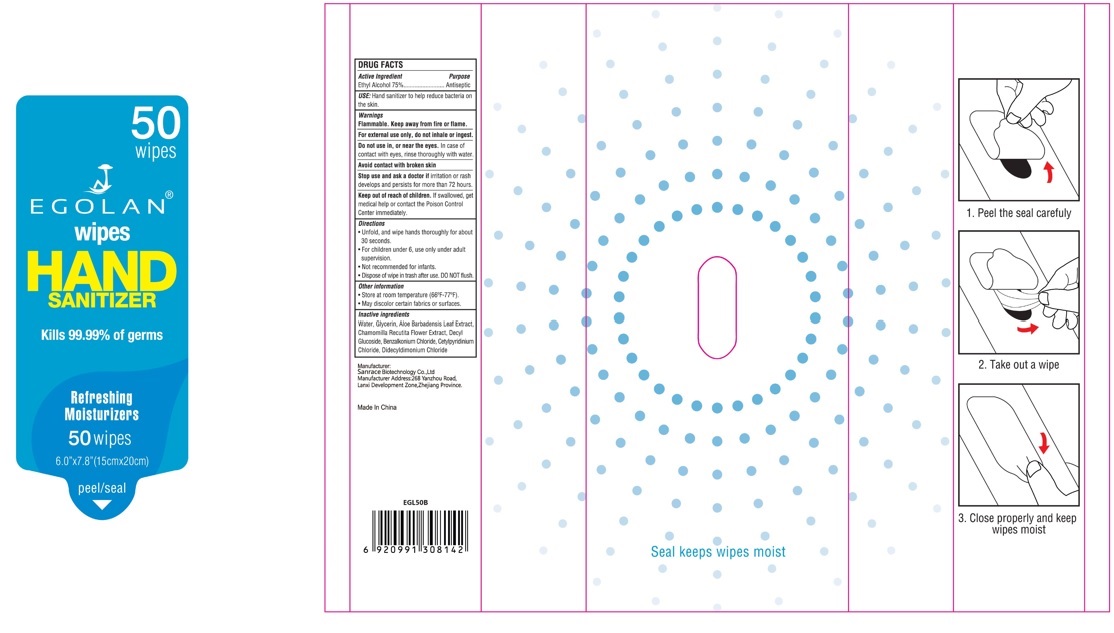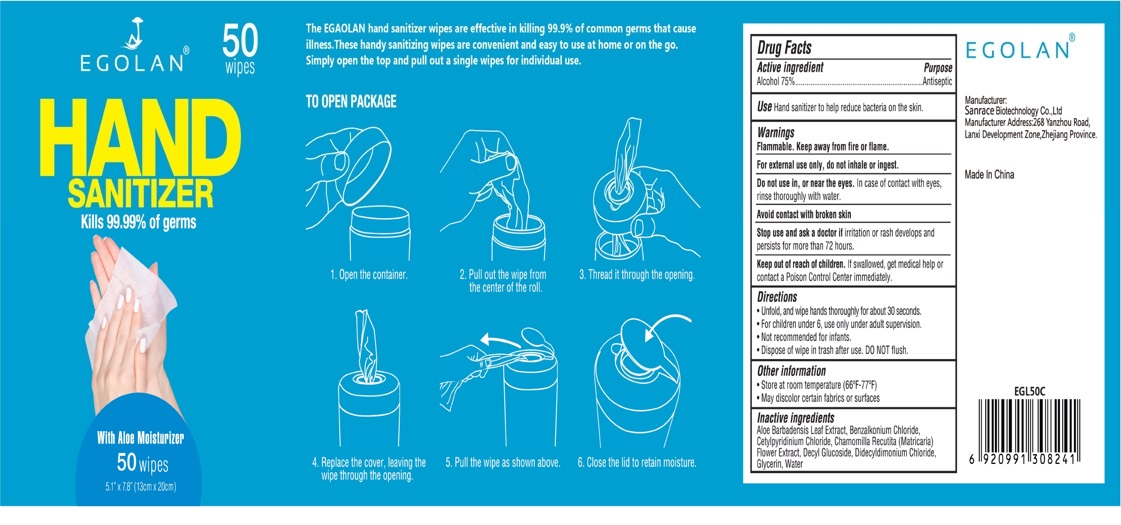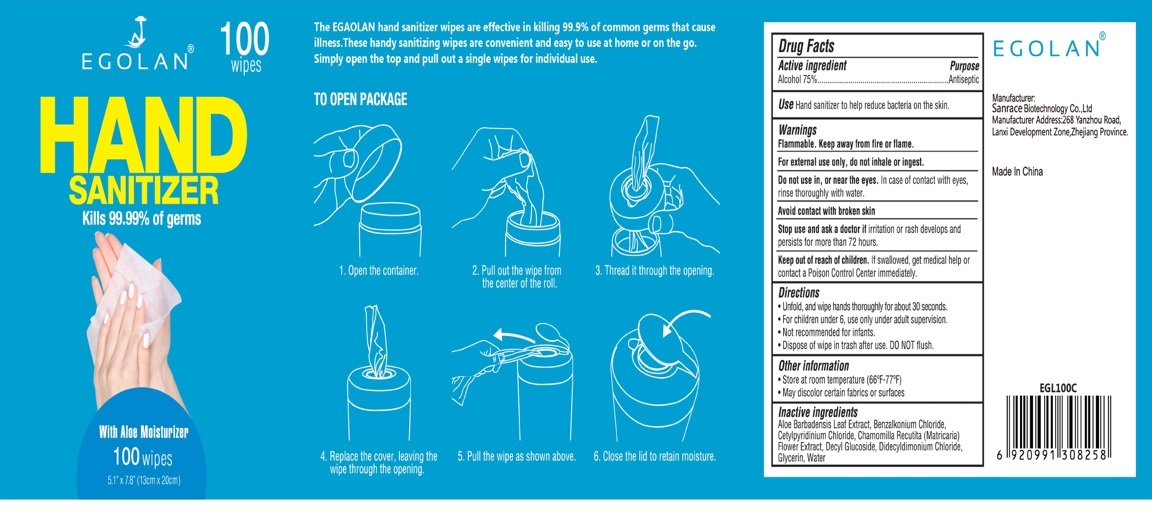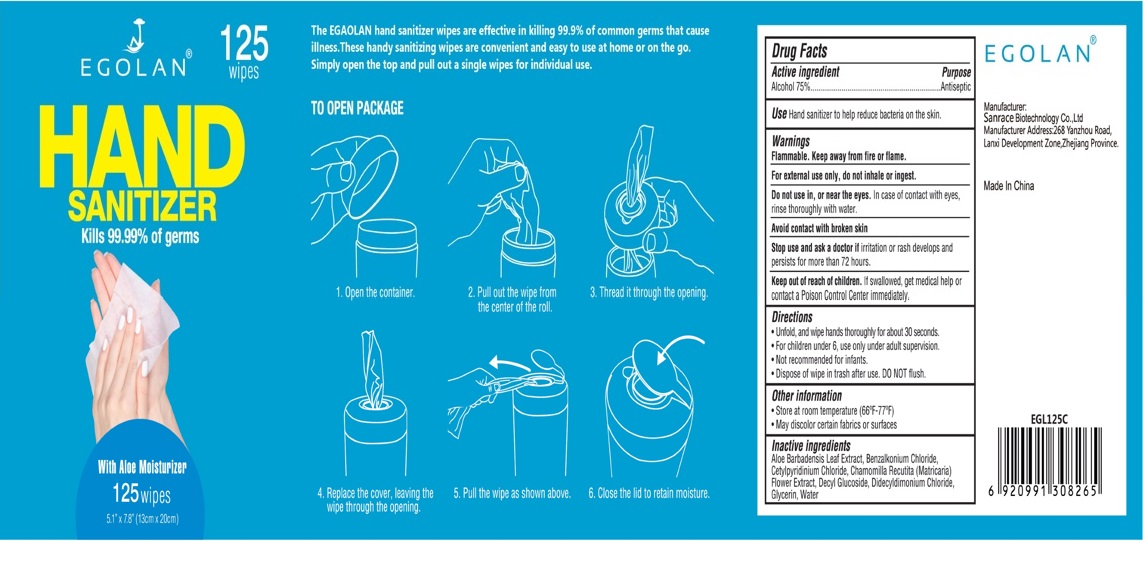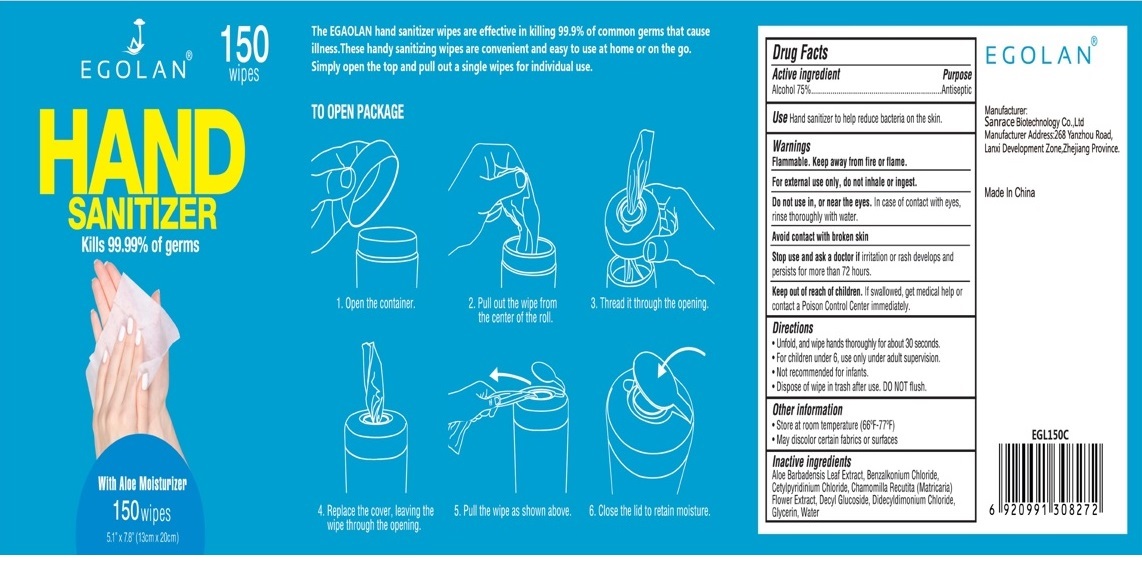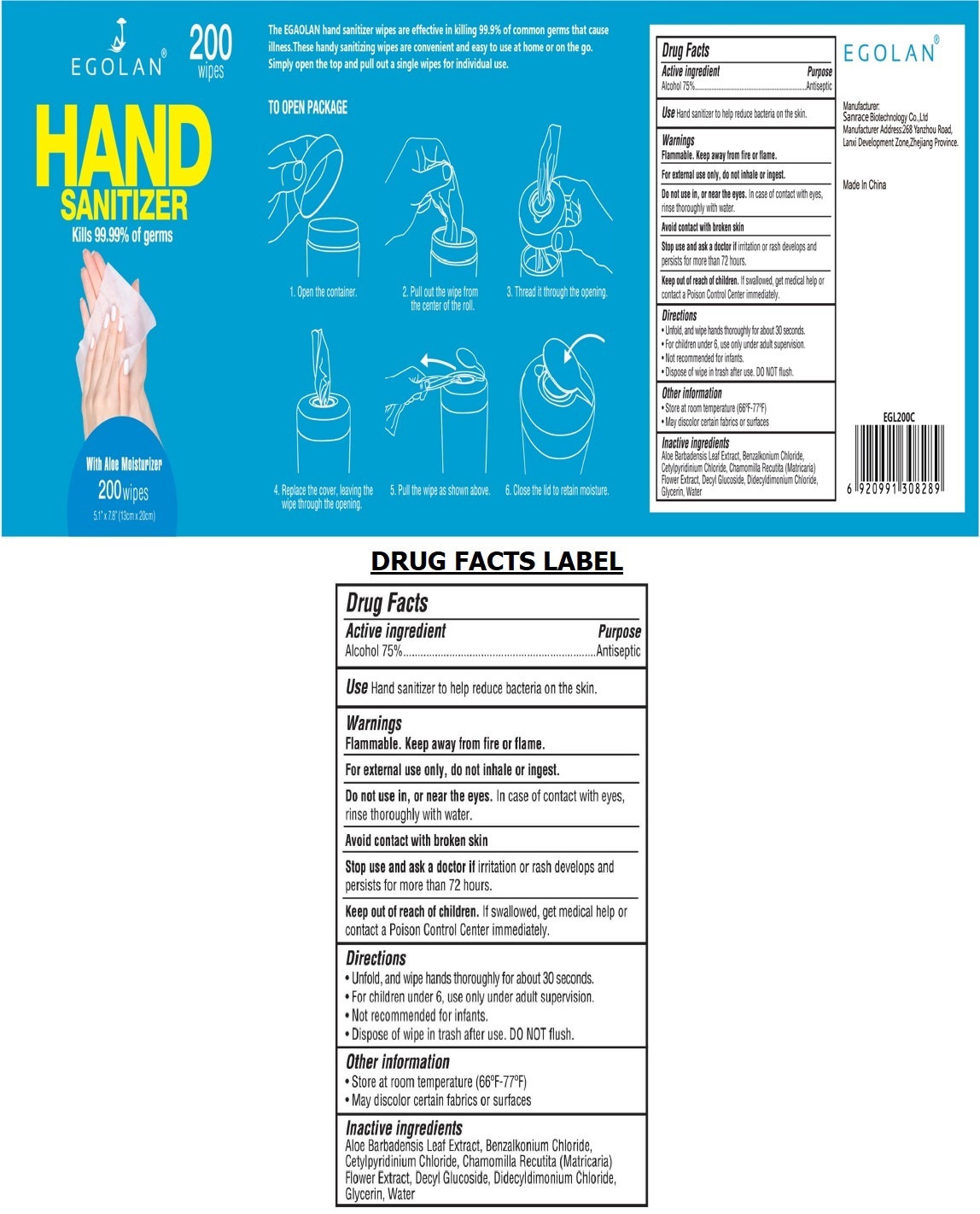 DRUG LABEL: EGOLAN Wipes HAND SANITIZER
NDC: 75448-030 | Form: CLOTH
Manufacturer: Sanrace Biotechnology Co., Ltd.
Category: otc | Type: HUMAN OTC DRUG LABEL
Date: 20200908

ACTIVE INGREDIENTS: ALCOHOL 75 mL/100 mL
INACTIVE INGREDIENTS: ALOE VERA LEAF; BENZALKONIUM CHLORIDE; CETYLPYRIDINIUM CHLORIDE; CHAMOMILE; DECYL GLUCOSIDE; DIDECYLDIMONIUM CHLORIDE; GLYCERIN; WATER

EGOLAN® HAND SANITIZER Wipes

Active ingredient

Alcohol 75%

Purpose

Antiseptic

INDICATIONS AND USAGE

Use Hand sanitizer to help reduce bacteria on the skin

Warnings

Flammable. Keep away from fire or flame.

For external use only, do not inhale or ingest.

Do not use in, or near the eyes. In case of contact with eyes, rinse thoroughly with water.

Avoid contact with broken skin

Stop use and ask a doctor if irritation or rash develops and persists for more than 72 hours.

Keep out of reach of children. If swallowed, get medical help or contact a Poison Control Center immediately.

Directions

• Unfold, and wipe hands thoroughly for about 30 seconds.

• For children under 6, use only under adult supervision.

• Not recommended for infants.

• Dispose of wipe in trash after use. DO NOT flush.

Other information

• Store at room temperature (66°F-77°F).

• May discolor certain fabrics or surfaces

Inactive ingredients

Aloe Barbadensis Leaf Extract, Benzalkonium Chloride, Cetylpyridinium Chloride, Chamomilla Recutita (Matricaria) Flower extract,

Decyl Glucoside, Didecyldimonium Cloride, Glycerin, water

Kills 99.99% of germs

With Aloe Moisturizer

Refreshing Moisturizers

The EGOLAN hand sanitizer wipes are effective in killing 99.9% of common germs that cause illness. These handy sanitizing wipes are convenient and easy to use at home or on the go. Simply open the top and pull out a single wipes for individual use.

TO OPEN PACKAGE

1. Open the container.

2. Pull out the wipe from the center of the roll.

3. Thread it through the opening.

4. Replace the cover, leaving the wipe through the opening.

5. Pull the wipe as shown above.

6. Close the lid to retain moisture.

Seal keeps wipes moist

1. Peel the seal carefully

2. Take out a wipe

3. Close properly and keep wipes moist

EGOLAN®

Manufacturer:

Sanrace Biotechnology Co., Ltd.

Manufacturer Address:268 Yanzhou Road,

Lanxi Development Zone, Zhejiang Province.

Made In China